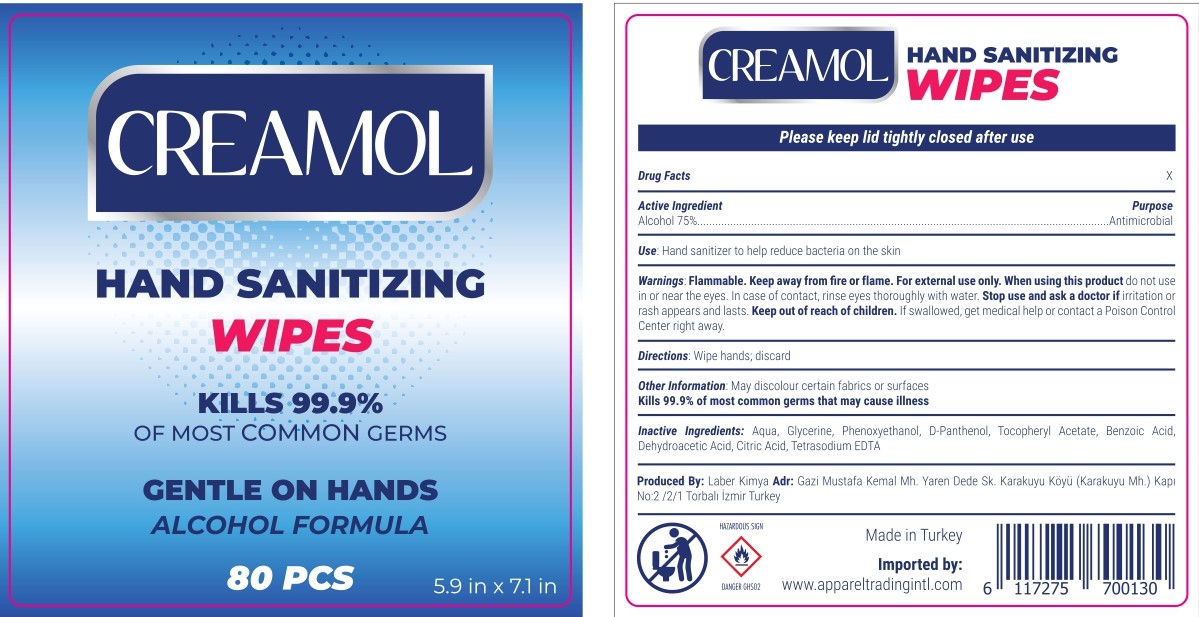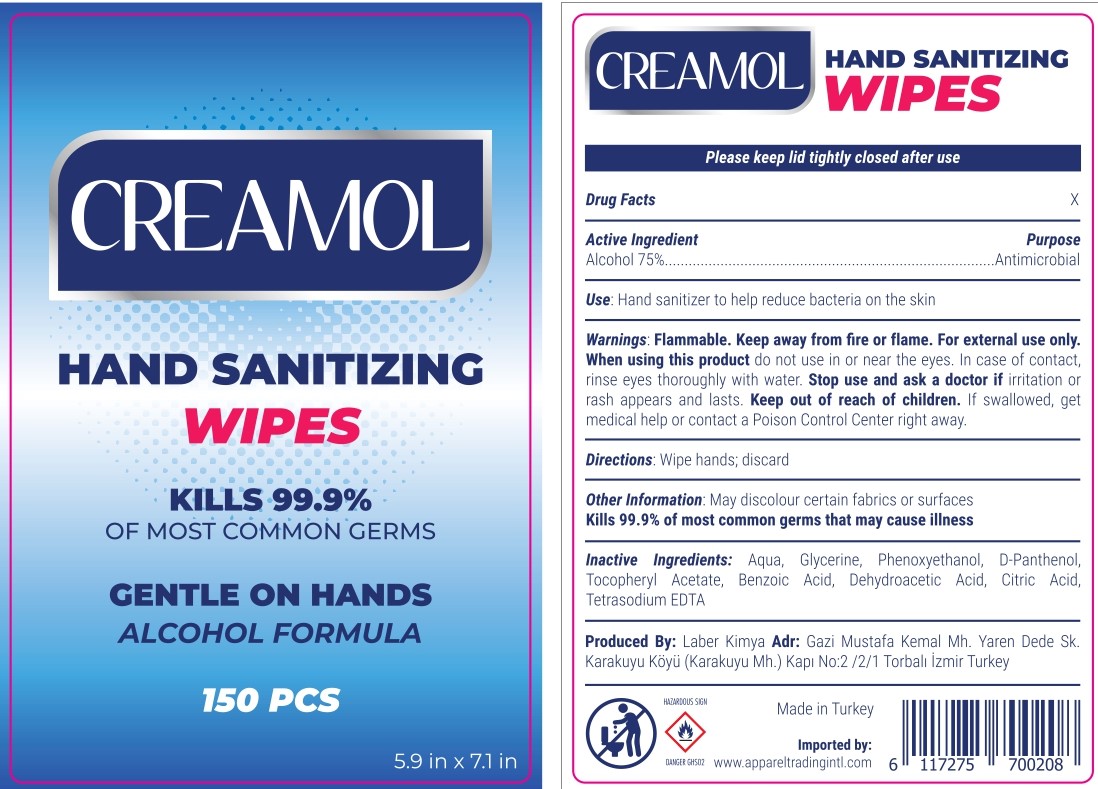 DRUG LABEL: Creamol Alcohol Wipes
NDC: 77892-0005 | Form: SWAB
Manufacturer: LABER KIMYA AR-GE SANAYI TICARET - LEVENT KAHRIMAN
Category: otc | Type: HUMAN OTC DRUG LABEL
Date: 20200824

ACTIVE INGREDIENTS: ALCOHOL 45 mg/100 mg; ISOPROPYL ALCOHOL 30 mg/100 mg; BENZALKONIUM CHLORIDE 0.13 mg/100 mg
INACTIVE INGREDIENTS: WATER; PANTHENOL; GLYCERIN; .ALPHA.-TOCOPHEROL, D-

Creamol Alcohol Wipes

ACTIVE INGREDIENT

Alcohol (45%), Isopropyl Alcohol (30%), Benzalkonium Chloride (0,13%) (w/w)

PURPOSE

Antiseptic

Directions

Used for hand and skin cleaning. Open the label and take one. Gently wipe your hands with an antibacterial wipe. It does not require rinsing after use.

INDICATIONS AND USAGE

It provides a practical cleaning without using water and soap when necessary. It helps reduce bacteria that potentially can cause disease. For use when soap and water are not available.

WARNINGS

For external use only. Flammable, keep away from fire and flame.

Do not use on open wounds and in children less than 2 months of age

WHEN USING

Keep out of eyes, ears, and mouth. In case of contact with eyes, rinse eyes throughly with water.

STOP USE

If irritation and redness develops and persist and in case of poisoning stop use and ask a doctor. Symptoms of Poisoning are dizziness, loss of consciousness and speech disorder.

Keep out of reach of children. If swallowed, get medical help or contact a Poison Control Center right away.

INACTIVE INGREDIENT

Aqua, Glycerine, Parfum, D-Panthenol, Tocopheryl Acetate

Other informations

Store between 15-30 ºC. Avoid freezing and excessive heat above 40ºC